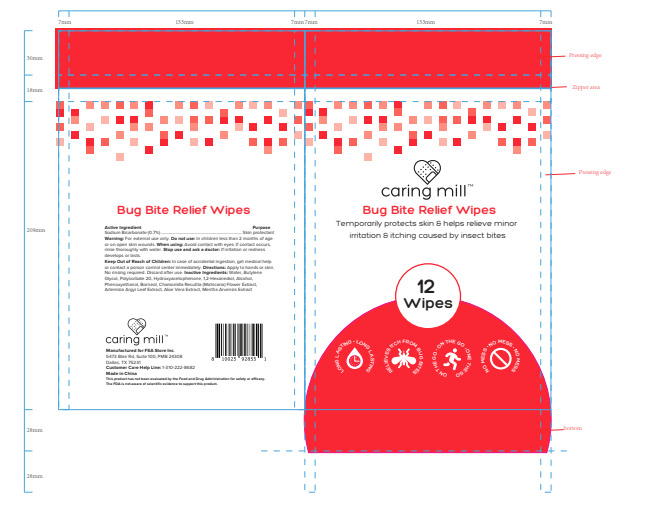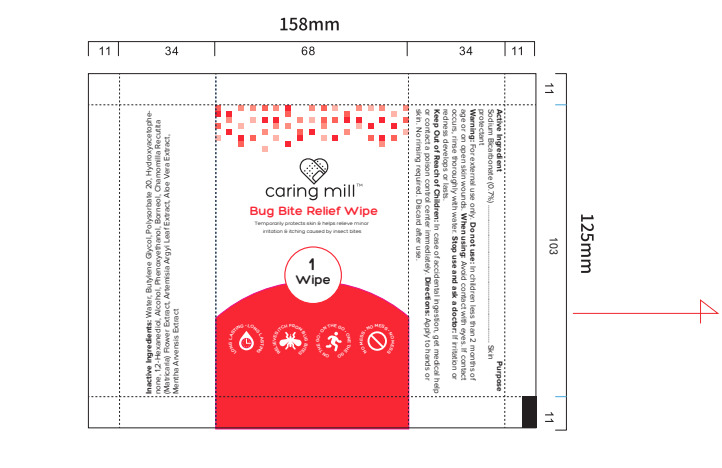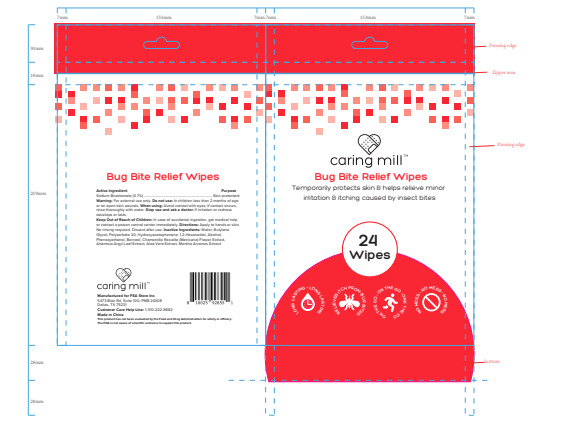 DRUG LABEL: Caring Mill Bug Bite Relief Wipes
NDC: 43116-037 | Form: CLOTH
Manufacturer: Shenzhen Shierjie Biological Engineering Co., LTD
Category: otc | Type: HUMAN OTC DRUG LABEL
Date: 20250108

ACTIVE INGREDIENTS: SODIUM BICARBONATE 0.7 U/100 U
INACTIVE INGREDIENTS: MENTHA ARVENSIS FLOWERING TOP; BUTYLENE GLYCOL; POLYSORBATE 20; HYDROXYACETOPHENONE; 1,2-HEXANEDIOL; ALCOHOL; ARTEMISIA ARGYI LEAF; AQUA; PHENOXYETHANOL; CHAMOMILE; ALOE VERA LEAF; BORNEOL

43116-037

Active Ingredient

SODIUM BICARBONATE 0.7%

Purpose

Skin protectant

Use

temporarily protects skin 8 helps relieve minor
irritation 8 itching caused by insect bites

Warnings

For external use only.

Do not use

●In children less than 2 months of age or on open skin wounds

When Using

Avoid contact with eyes
If contact occurs，rinse thoroughly with water

Stop Use

If irritation or redness develops or lasts.

Ask Doctor

If there is any discomfort during use, please stop using immediately.

Keep Oot Of Reach Of Children

In case of accidental ingestion, get medical help or contact a poison control center immediately.

Directions

Apply to hands or skin. No rinising required. Discard after use.

Inactive ingredients

Water, Butylene Glycol, Polysorbate 20, Hydroxyacetophenone, 1,2-Hexanediol, Alcohol,
Phenoxyethanol, Borneol, Chamomilla Recutita (Matricaria) Flower Extract,
Artemisia Argyi Leaf Extract, Aloe Vera Extract, Mentha Arvensis Extract .